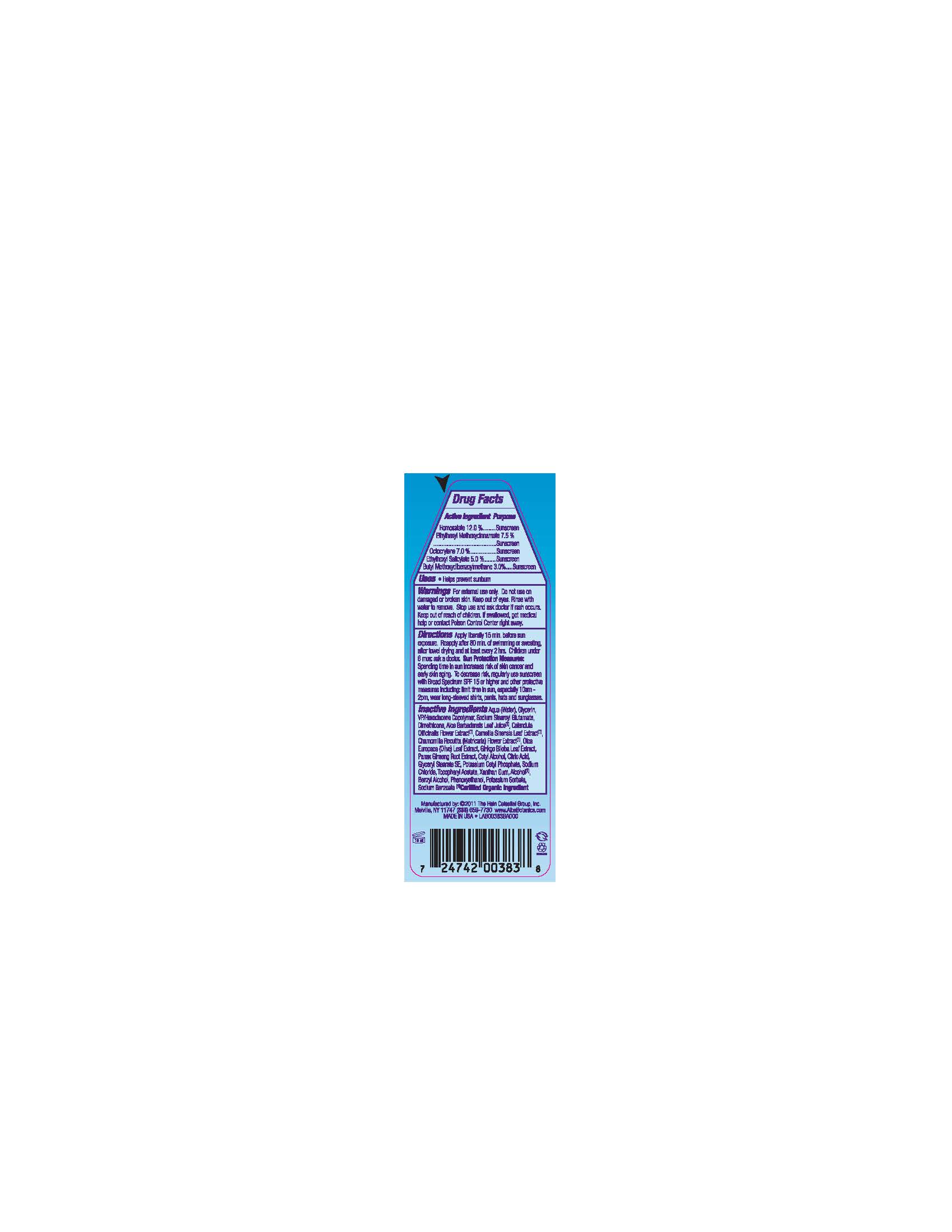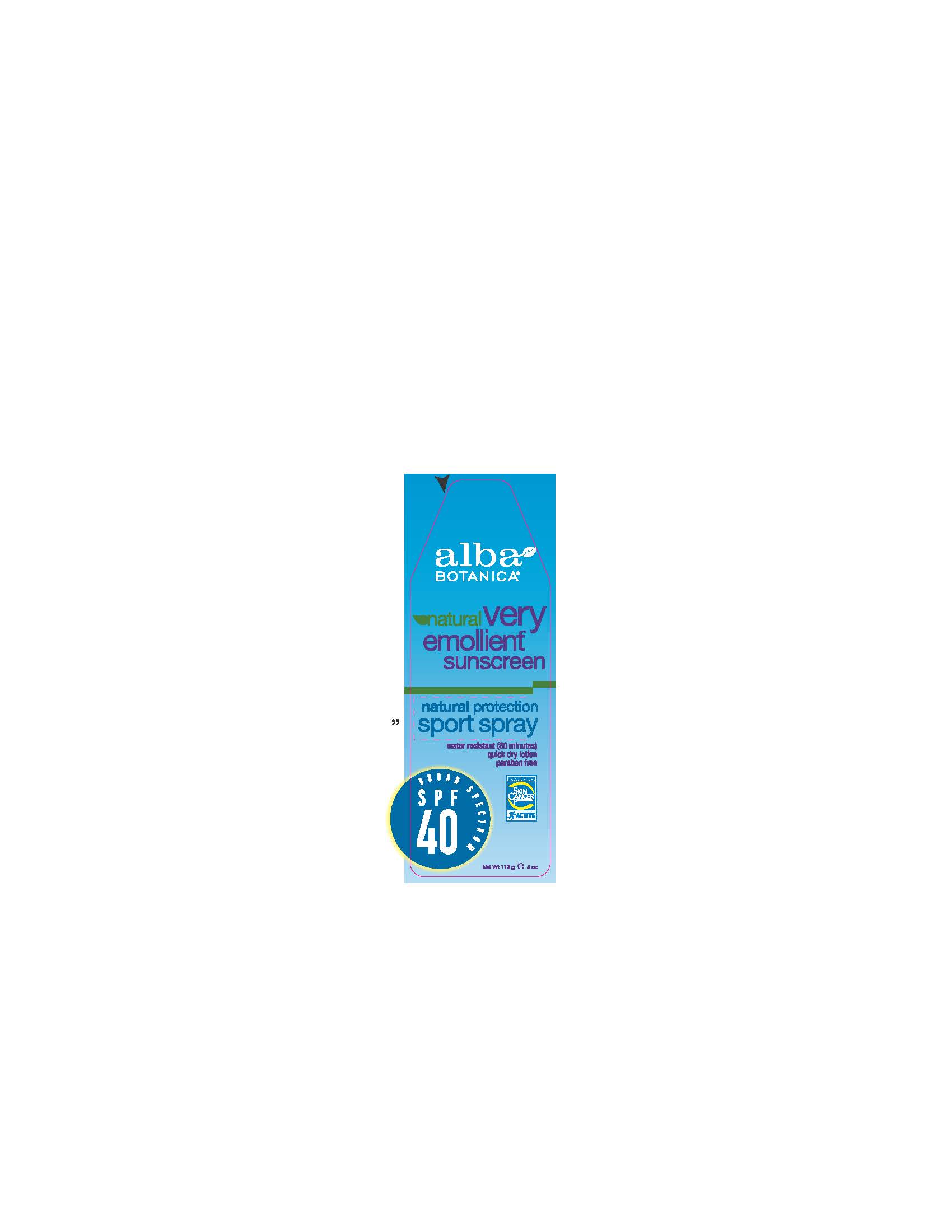 DRUG LABEL: Alba Botanica Natural Very Emollient Sunscreen Sport Spray SPF40
NDC: 61995-2383 | Form: LOTION
Manufacturer: The Hain Celestial Group, Inc.
Category: otc | Type: HUMAN OTC DRUG LABEL
Date: 20120508

ACTIVE INGREDIENTS: HOMOSALATE 12 g/100 g; OCTINOXATE  7.5 g/100 g; OCTOCRYLENE 7.0 g/100 g; OCTISALATE  5.0 g/100 g; AVOBENZONE  3.0 g/100 g
INACTIVE INGREDIENTS: WATER; GLYCERIN; SODIUM STEAROYL GLUTAMATE; DIMETHICONE; ALOE VERA LEAF; CALENDULA OFFICINALIS FLOWER ; GREEN TEA LEAF; CHAMOMILE ; OLEA EUROPAEA LEAF; GINKGO; ASIAN GINSENG; CETYL ALCOHOL ; GLYCERYL MONOSTEARATE; CITRIC ACID MONOHYDRATE ; POTASSIUM CETYL PHOSPHATE; SODIUM CHLORIDE; .ALPHA.-TOCOPHEROL ACETATE; XANTHAN GUM ; ALCOHOL ; BENZYL ALCOHOL ; PHENOXYETHANOL; POTASSIUM SORBATE ; SODIUM BENZOATE

Drug Facts

ACTIVE INGREDIENT

Homosalate 12.0%

Ethylhexyl Methoxycinnamate 7.5%

Octocrylene 7.0%

Ethylhexyl Salicylate 5.0%

Butyl Methoxybenzoylmethane 3.0%

PURPOSE

Sunscreen

INDICATIONS AND USAGE

- Helps prevent sunburn

WARNINGS

For external use only. Do not use on damaged or broken skin. Keep out of eyes.Rinse with water to remove. Stop use and ask a doctor if skin rash occurs.

Keep out of reach of children. If swallowed, get medical help or contact a Poison Control Center right away

DOSAGE AND ADMINISTRATION

Apply liberally 15 minutes before sun exposure. Reapply after 80 min of swimming or sweating,after towel drying and at lease every two hrs. Children under 6 mos ask a doctor.
Skin protection measures: Spending time in the sun increases your risk of skin cancer and early skin aging. To decrease a risk,regularly use a Sunscreen with Broad Spectrum SPF 15 or higher and other protective measures including: limit time in sun, especially 10am- 2pm, wear long- sleeved shirts,pants, hats and sunglasses.

INACTIVE INGREDIENT

Aqua (Water), Aloe Barbadensis Leaf Juice (1), Glycerin, VP/Hexadecene Copolymer, Sodium Stearoyl Glutamate, Calendula Officinalis Flower Extract (1), Camellia Sinensis Leaf Extract (1), Chamomilla Recuitita (Matricaria) Flower Extract (1), Olea Europaea (Olive) Leaf Extract, Panax Ginseng Root Extract (1), Gingko Biloba Root Extract, Cetyl Alcohol, Citric Acid, Glyceryl Stearate SE, Potassium Cetyl Phosphate, Sodium Chloride, Tocopheryl Acetate, Xanthan Gum, Alcohol (1), Benzyl Alcohol, Phenoxyethanol, Potassium Sorbate, Sodium Benzoate.
(1) Certified Organic Ingredient

QUESTIONS

888-659-7730, www.AlbaBotanica.com